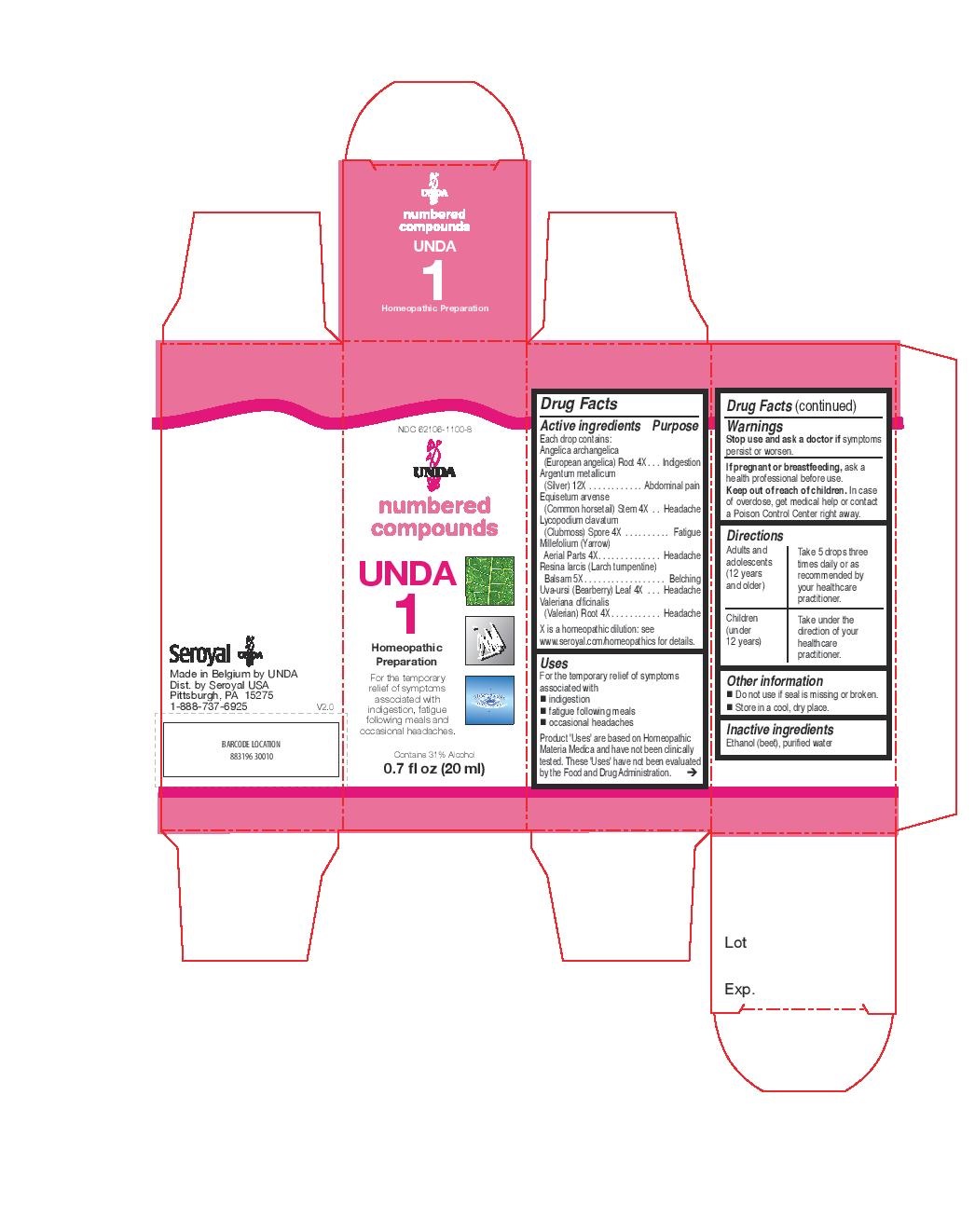 DRUG LABEL: Unda 1
NDC: 62106-1100 | Form: LIQUID
Manufacturer: Seroyal USA
Category: homeopathic | Type: HUMAN OTC DRUG LABEL
Date: 20221107

ACTIVE INGREDIENTS: ACHILLEA MILLEFOLIUM 4 [hp_X]/20 mL; ARCTOSTAPHYLOS UVA-URSI LEAF 4 [hp_X]/20 mL; VALERIAN 4 [hp_X]/20 mL; ANGELICA ARCHANGELICA ROOT 4 [hp_X]/20 mL; EQUISETUM ARVENSE TOP 4 [hp_X]/20 mL; LYCOPODIUM CLAVATUM SPORE 4 [hp_X]/20 mL; LARIX DECIDUA RESIN 5 [hp_X]/20 mL; SILVER 12 [hp_X]/20 mL
INACTIVE INGREDIENTS: WATER; ALCOHOL

Unda 1

Uses
For the temporary relief of symptoms associated with
indigestion
fatigue following meals
occasional headaches

Warnings
Stop use and ask a doctor if symptoms
persist or worsen.
If pregnant or breastfeeding, ask a
health professional before use.
Keep out of reach of children. In case
of overdose, get medical help or contact
a Poison Control Center right away.

Keep out of reach of children.

Active ingredients
Each drop contains:
Angelica archangelica (European angelica) Root 4X
Argentum metallicum (Silver) 12X
Equisetum arvense (Common horsetail) Stem 4X
Lycopodium clavatum (Clubmoss) Spore 4X
Millefolium (Yarrow) Aerial Parts 4X
Resina larcis (Larch turnpentine) Balsam 5X
Uva-ursi (Bearberry) Leaf 4X
Valeriana officinalis (Valerian) Root 4X

Inactive ingredients
Ethanol (beet), purified water

Uses
For the temporary relief of symptoms associated with
indigestion
fatigue following meals
occasional headaches

Directions

Adults and adolescents (12 years and older)

Take 5 drops three times daily or as recommended by your healthcare practitioner.

Children (under 12 years)

Take under the direction of your healthcare practitioner.

Directions

Adults and adolescents (12 years and older)

Take 5 drops three times daily or as recommended by your healthcare practitioner.

Children (under 12 years)

Take under the direction of your healthcare practitioner.

Stop use and ask a doctor if symptoms persist or wosen.

Do not use if seal is missing or broken.

Store in a cool dry place.

PACKAGE LABEL

NDC 62106-1100-8

UNDA

numbered compounds

UNDA 1

Homeopathic Preparation

For the temporary
relief of symptoms associated with
indigestion, fatigue following meals

and occasional headaches.

Contains 31% Alcohol

0.7 fl oz (20 ml)